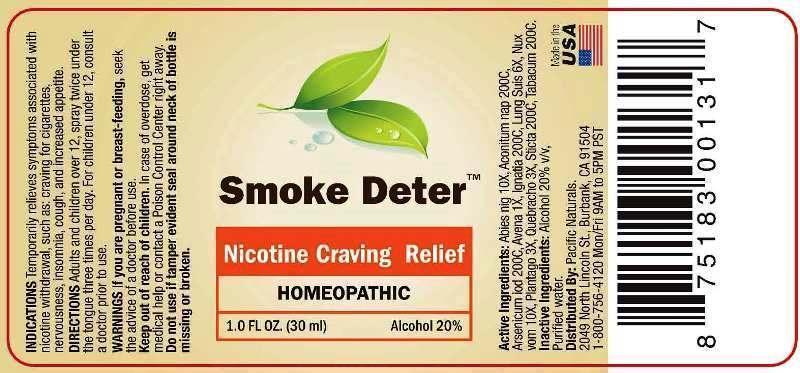 DRUG LABEL: Smoke Deter
NDC: 43695-0002 | Form: SPRAY
Manufacturer: Pacific Naturals
Category: homeopathic | Type: HUMAN OTC DRUG LABEL
Date: 20141218

ACTIVE INGREDIENTS: PICEA MARIANA RESIN 10 [hp_X]/1 mL; ACONITUM NAPELLUS 200 [hp_C]/1 mL; ARSENIC TRIIODIDE 200 [hp_C]/1 mL; AVENA SATIVA FLOWERING TOP 1 [hp_X]/1 mL; STRYCHNOS IGNATII SEED 200 [hp_C]/1 mL; SUS SCROFA LUNG 6 [hp_X]/1 mL; STRYCHNOS NUX-VOMICA SEED 10 [hp_X]/1 mL; PLANTAGO MAJOR 3 [hp_X]/1 mL; ASPIDOSPERMA QUEBRACHO-BLANCO BARK 3 [hp_X]/1 mL; LOBARIA PULMONARIA 200 [hp_C]/1 mL; TOBACCO LEAF 200 [hp_C]/1 mL
INACTIVE INGREDIENTS: WATER; ALCOHOL

DRUG FACTS:

ACTIVE INGREDIENTS:

ABIES NIGRA 10X, ACONITUM NAPELLUS 200C, ARSENICUM IODATUM 200C, AVENA SATIVA 1X, IGNATIA AMARA 200C, LUNG SUIS 6X, NUX VOMICA 10X, PLANTAGO MAJOR 3X, QUEBRACHO 3X, STICTA PULMONARIA 200C, TABACUM 200C

INDICATIONS:

Temporarily relieves symptoms associated with nicotine withdrawal, such as: craving for cigarettes, nervousness, insomnia, cough, and increased appetite.

WARNINGS:

If you are pregnant or breast-feeding, seek the adivce of a doctor before use.

Keep out of reach of children. In case of overdose, get medical help or contact a Poison Control Center right away.

Do not use if tamper evident seal around neck of bottle is missing or broken.

Keep out of reach of children. In case of overdose, get medical help or contact a Poison Control Center right away.

DIRECTIONS:

Adults and children over 12, spray twice under the tongue three times per day. For children under 12, consult a doctor prior to use.

INDICATIONS:

Temporarily relieves symptoms associated with nicotine withdrawal, such as: craving for cigarettes, nervousness, insomnia, cough, and increased appetite.

INACTIVE INGREDIENTS:

Alcohol 20% v/v, Purified water.

QUESTIONS:

Distributed By: Pacific Naturals.

2049 North Lincoln St., Burbank, CA 91504

1-800-756-4120 Mon/Fri 9AM to 5PM PST

PACKAGE LABEL DISPLAY:

Smoke Deter

Nicotine Craving Relief

HOMEOPATHIC

1.0 FL OZ. (30 ml